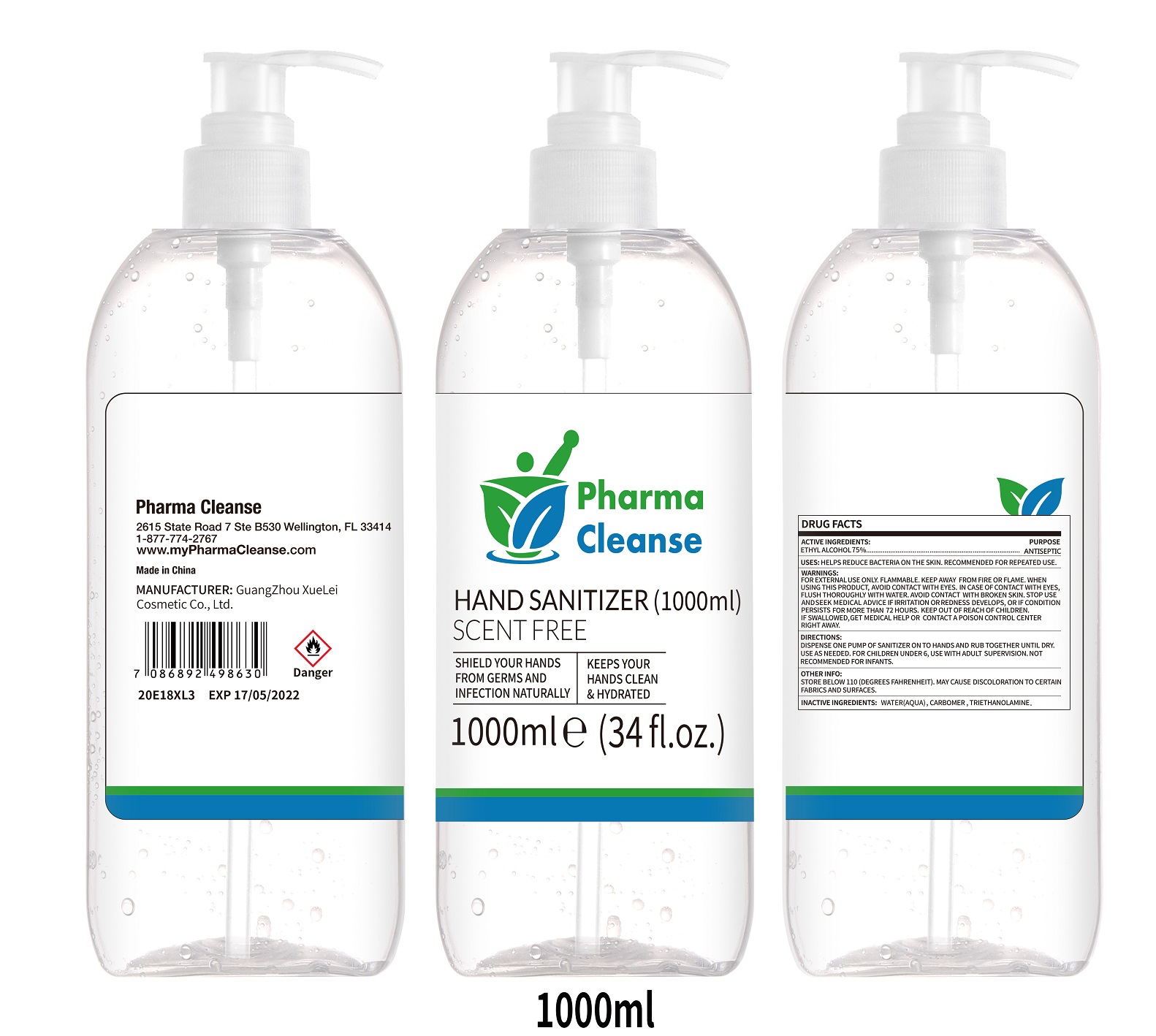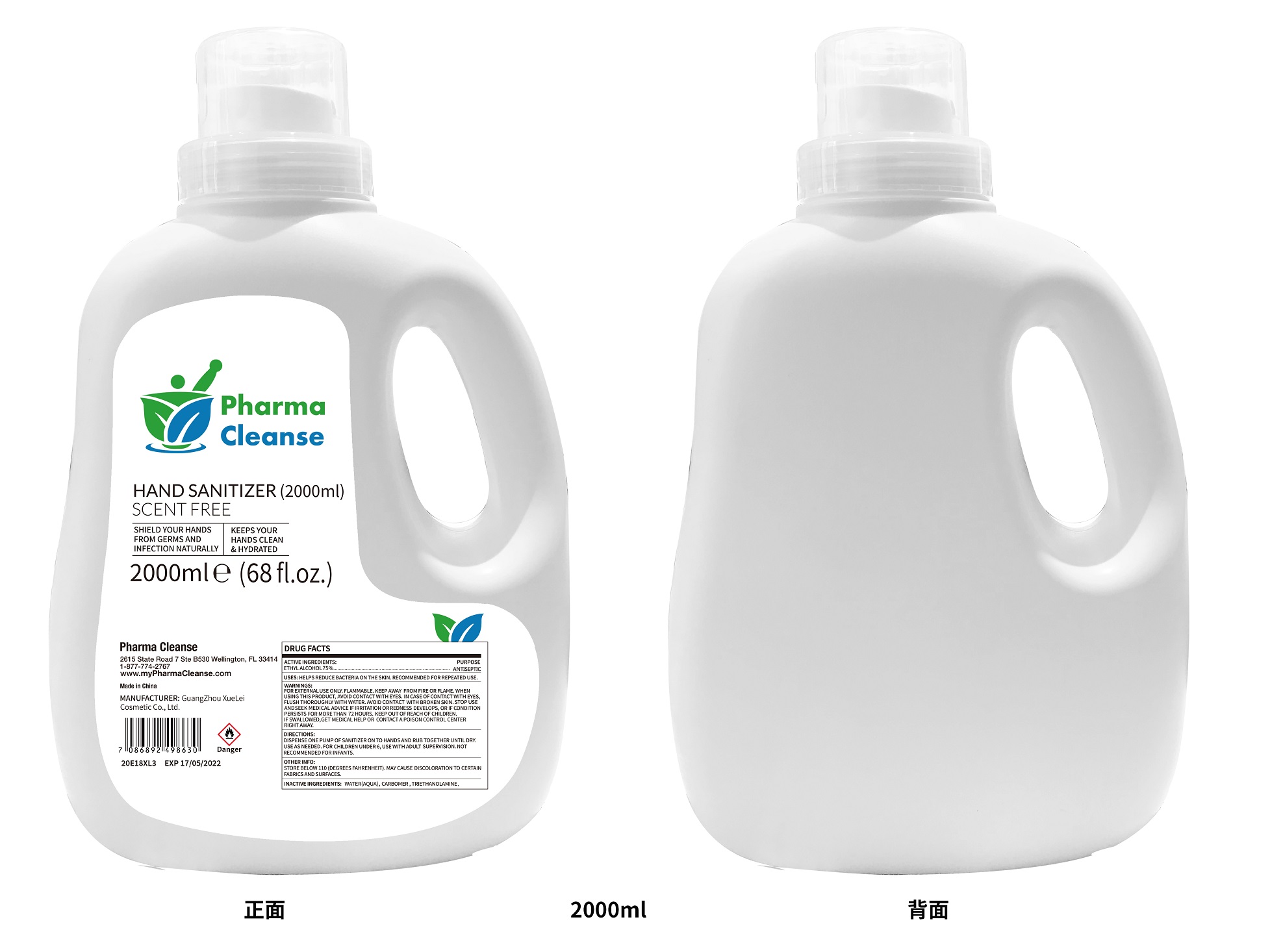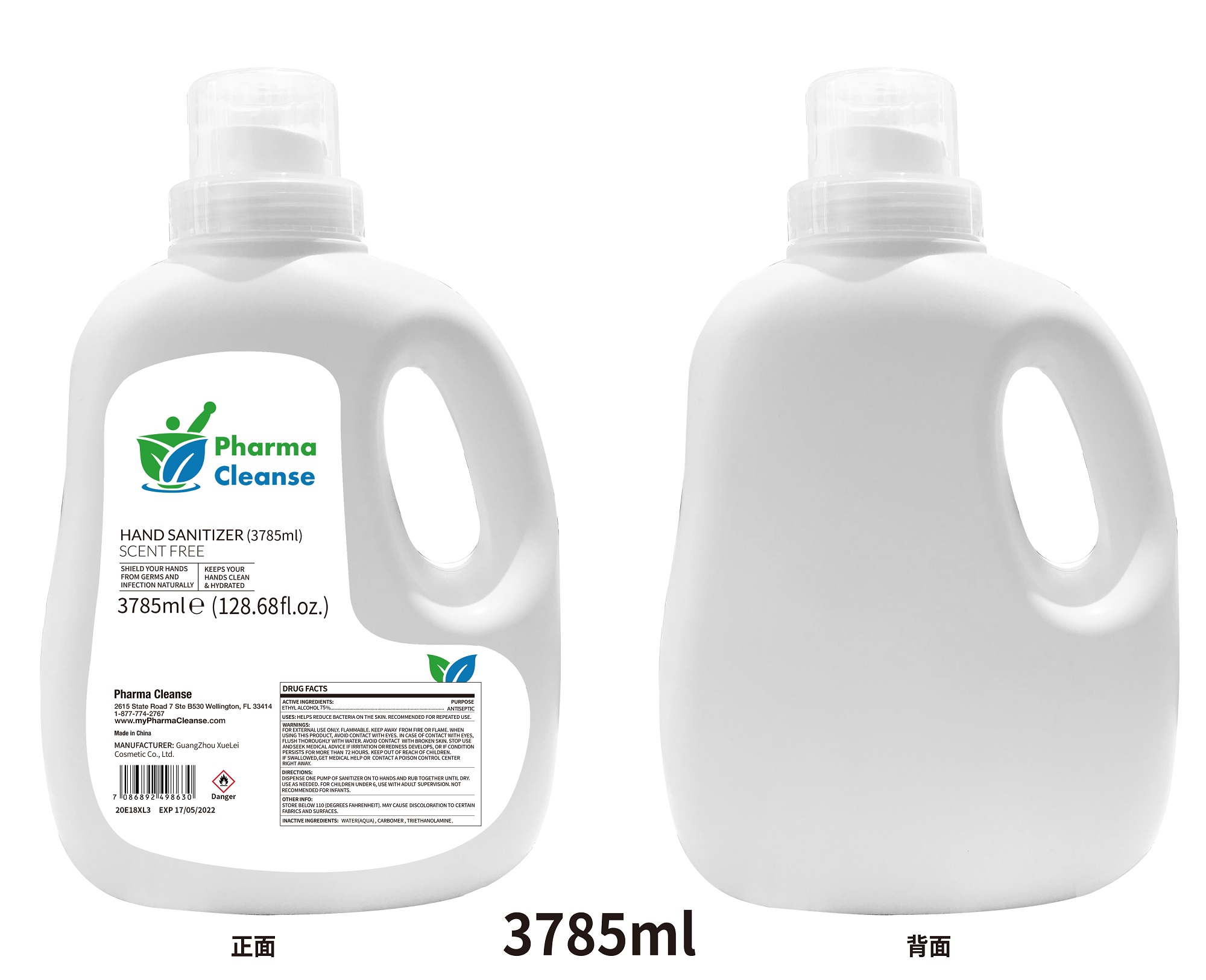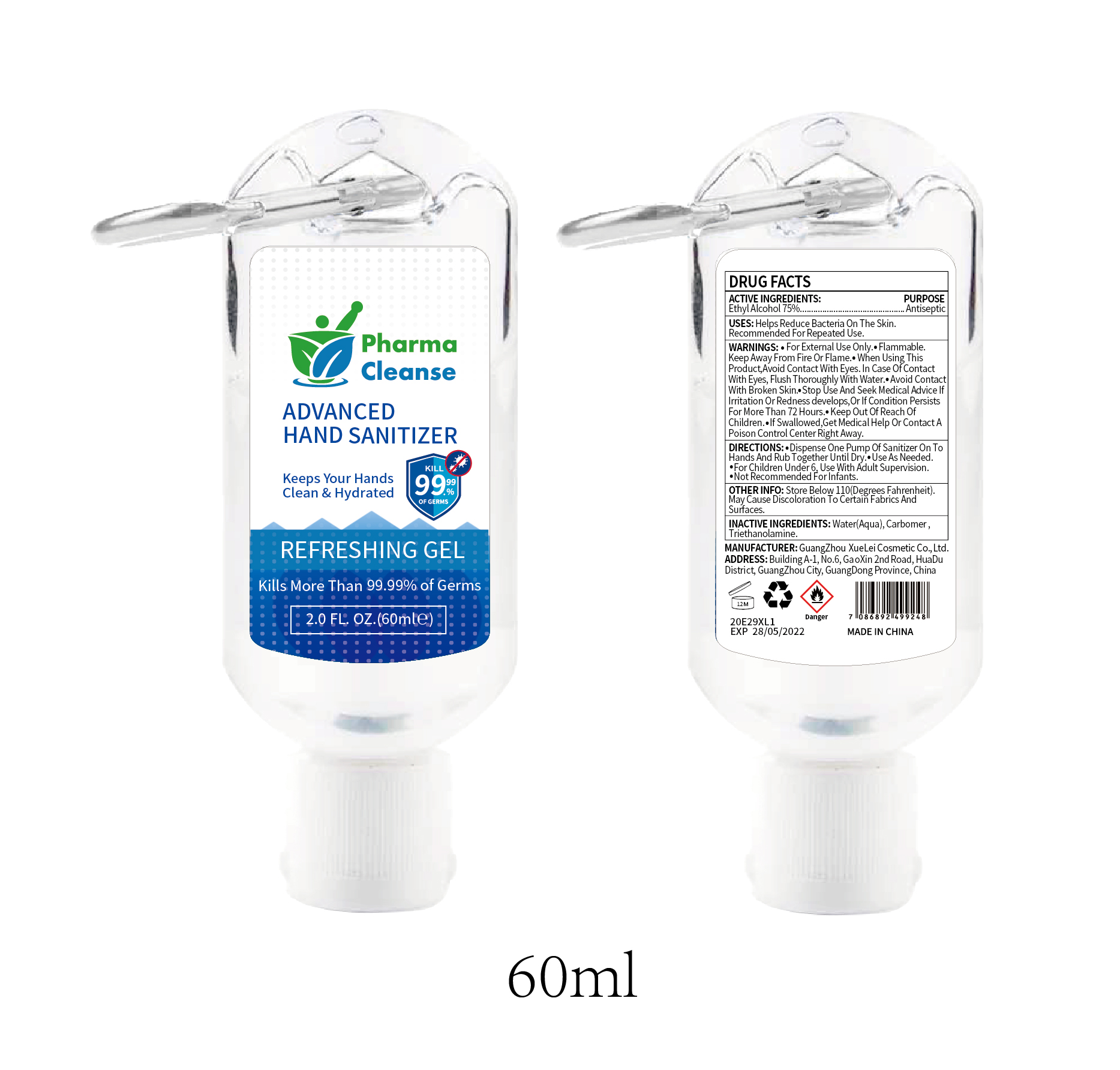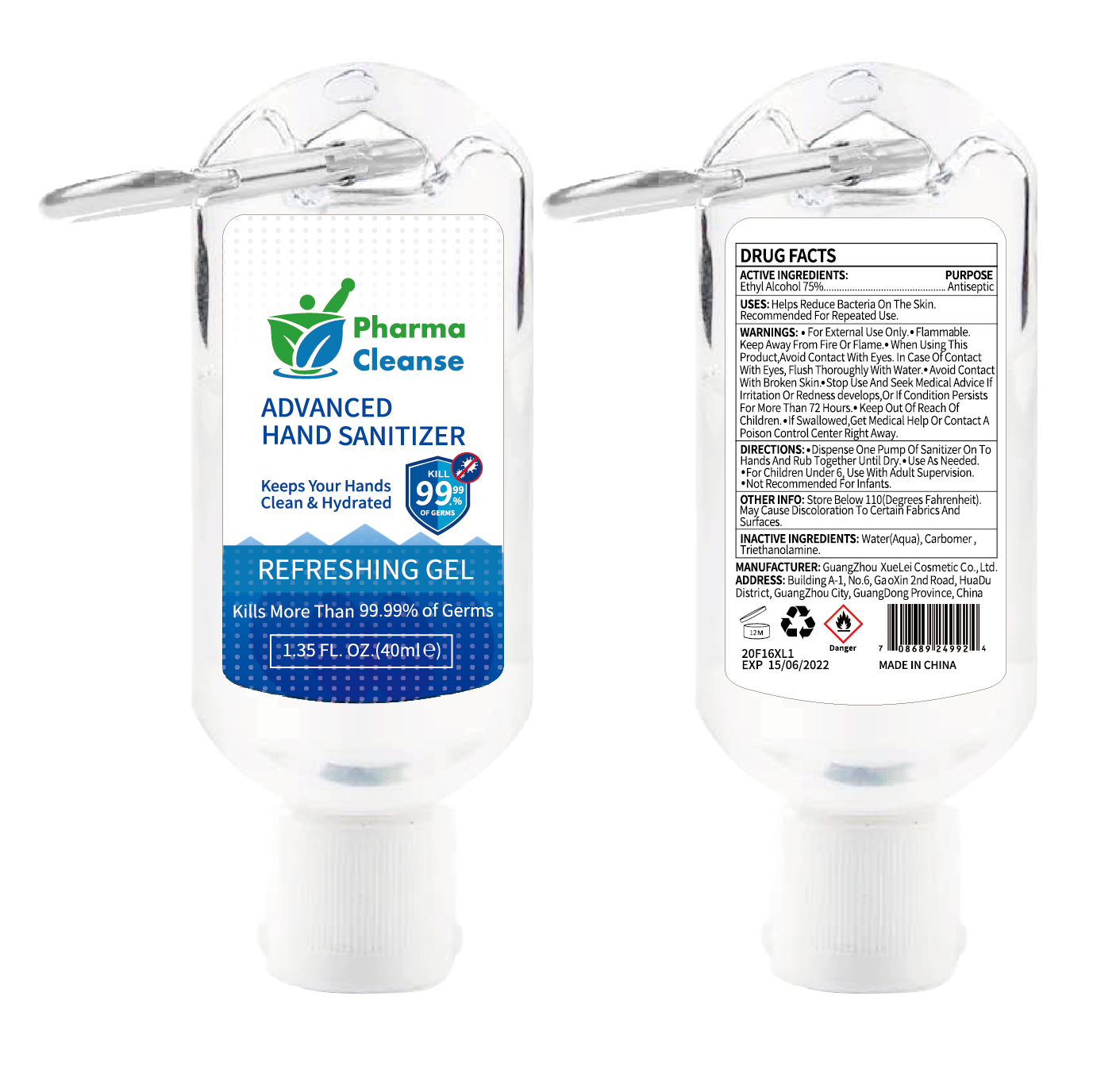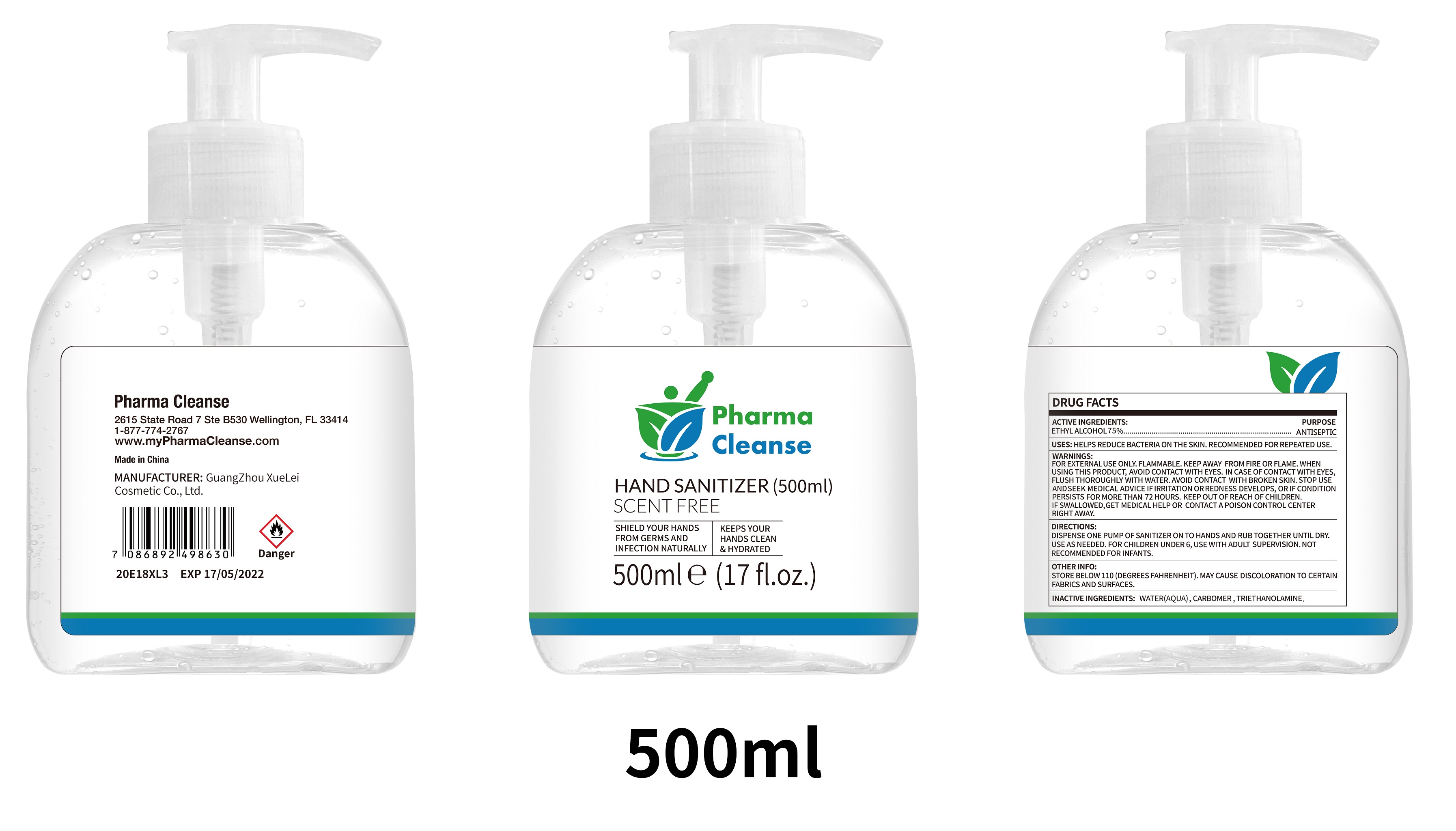 DRUG LABEL: Pharma Cleanse HAND SANITIZER
NDC: 78528-001 | Form: GEL
Manufacturer: Ballistic LLC
Category: otc | Type: HUMAN OTC DRUG LABEL
Date: 20211108

ACTIVE INGREDIENTS: ALCOHOL 75 mL/100 mL
INACTIVE INGREDIENTS: WATER 22.19 g/100 mL; CARBOMER HOMOPOLYMER TYPE B (ALLYL PENTAERYTHRITOL CROSSLINKED) 0.4 g/100 mL; TROLAMINE 0.22 g/100 mL

Pharma Cleanse HAND SANITIZER

ACTIVE INGREDIENTS:

ETHYL ALCOHOL 75%

PURPOSE

ANTISEPTIC

USES:

HELPS REDUCE BACTERIA ON THE SKIN. RECOMMENDED FOR REPEATED USE.

WARNINGS:

FOR EXTERNAL USE ONLY. FLAMMABLE. KEEP AWAY FROM FIRE OR FLAME. WHEN USING THIS PRODUCT, AVOID CONTACT WITH EYES. IN CASE OF CONTACT WITH EYES, FLUSH THOROUGHLY WITH WATER. AVOID CONTACT WITH BROKEN SKIN. STOP USE AND SEEK MEDICAL ADVICE IF IRRITATION OR REDNESS DEVELOPS, OR IF CONDITION PERSISTS FOR MORE THAN 72 HOURS. KEEP OUT OF REACH OF CHILDREN. IF SWALLOWED, GET MEDICAL HELP OR CONTACT A POISON CONTROL CENTER RIGHT AWAY.

KEEP OUT OF REACH OF CHILDREN. IF SWALLOWED, GET MEDICAL HELP OR CONTACT A POISON CONTROL CENTER RIGHT AWAY.

DIRECTIONS:

DISPENSE ONE PUMP OF SANITIZER ON TO HANDS AND RUB TOGETHER UNTIL DRY. USE AS NEEDED. FOR CHILDREN UNDER 6, USE WITH ADULT SUPERVISION. NOT RECOMMENDED FOR INFANTS.

OTHER INFO:

STORE BELOW 110 (DEGREES FAHRENHEIT). MAY CAUSE DISCOLORATION TO CERTAIN FABRICS AND SURFACES.

INACTIVE INGREDIENTS:

WATER (AQUA), CARBOMER, TRIETHANOLAMINE.

Package Label

40ml, NDC: 78528-001-01

60ml, NDC: 78528-001-02

500ml, NDC: 78528-001-03

1000ml, NDC: 78528-001-04

2000ml, NDC: 78528-001-05

3785ml, NDC: 78528-001-06